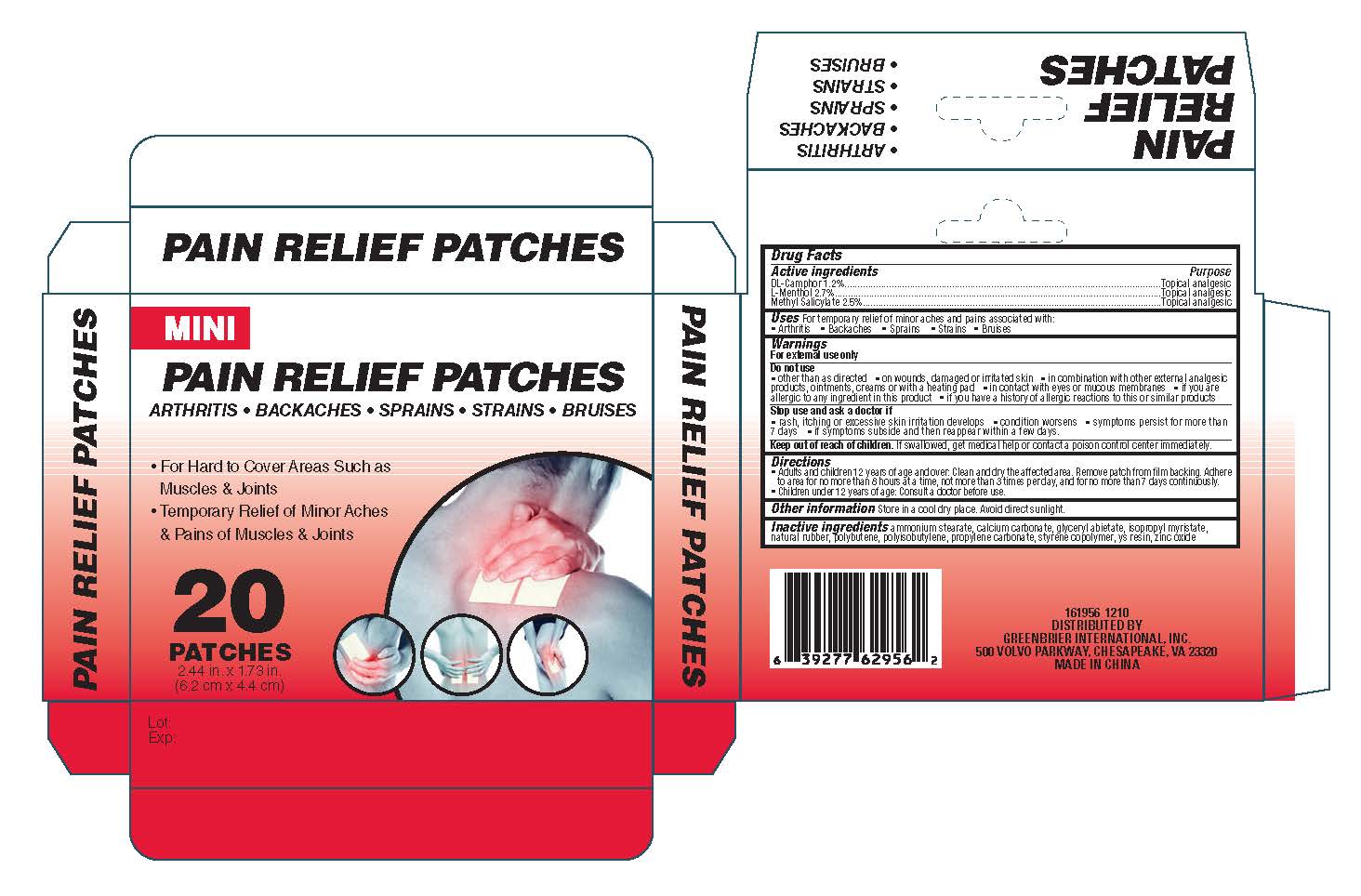 DRUG LABEL: Mini Pain Relief
NDC: 53043-003 | Form: PATCH
Manufacturer: Shanghai Aquagel Bio-Plymer Co., Ltd
Category: otc | Type: HUMAN OTC DRUG LABEL
Date: 20121226

ACTIVE INGREDIENTS: CAMPHOR (SYNTHETIC) 1.2 mg/1 1; LEVOMENTHOL 2.7 mg/1 1; METHYL SALICYLATE 2.5 mg/1 1
INACTIVE INGREDIENTS: AMMONIUM STEARATE; CALCIUM CARBONATE; GLYCERYL ABIETATE; ISOPROPYL MYRISTATE; NATURAL LATEX RUBBER; POLYBUTENE (1400 MW); POLYISOBUTYLENE (1000 MW); PROPYLENE CARBONATE; STYRENE; ZINC OXIDE

Drug Facts

INACTIVE INGREDIENT

Inactive ingredients Ammonium Stearate, Calcium Carbonate, Glyceryl Abietate, Isopropyl Myristate, Natural
Rubber,Polybutene, Polyisobutylene, Propylene Carbonate, Styrene Copolymer, YS Resin, Zinc Oxide

Active ingredients
DL-Camphor 1.2%
L-Menthol 2,.%
Methyl Salicylate 2.5%

Purpose

Topical Analgesic

Keep out of reach of children. If swallowed, get medical help or contact a poison control center immediately

Do not use
other than as directed on wounds, damaged or irritated skin in combination with other
external analgesic products, ointments, creams or with a heating pad. in contact with eyes or mucous
membranes. if you are allergic to any ingredient in this product or if you have a history of allergic reactions to this
or similar products

Stop Use and ask a
doctor if
rash, itching or excessive skin irritation develops
condition worsens
symptoms persist for more
than 7 days
if symptoms
subside and then reappear within a few days.

Warnings
For External Use Only

Directions
Adults and children 12 years of age and over: Clean and dry the affected area. Remove
patch from film backing. Adhere to area for no more than 8 hours at a time, not more than 3 times per day, and for no more
than 7 days continuously. Children under 12 years of age: Consult a doctor before use.

Uses
For temporary relief of minor aches and pains associated with:
Arthritis
Backaches
Sprains
Strains
Bruises